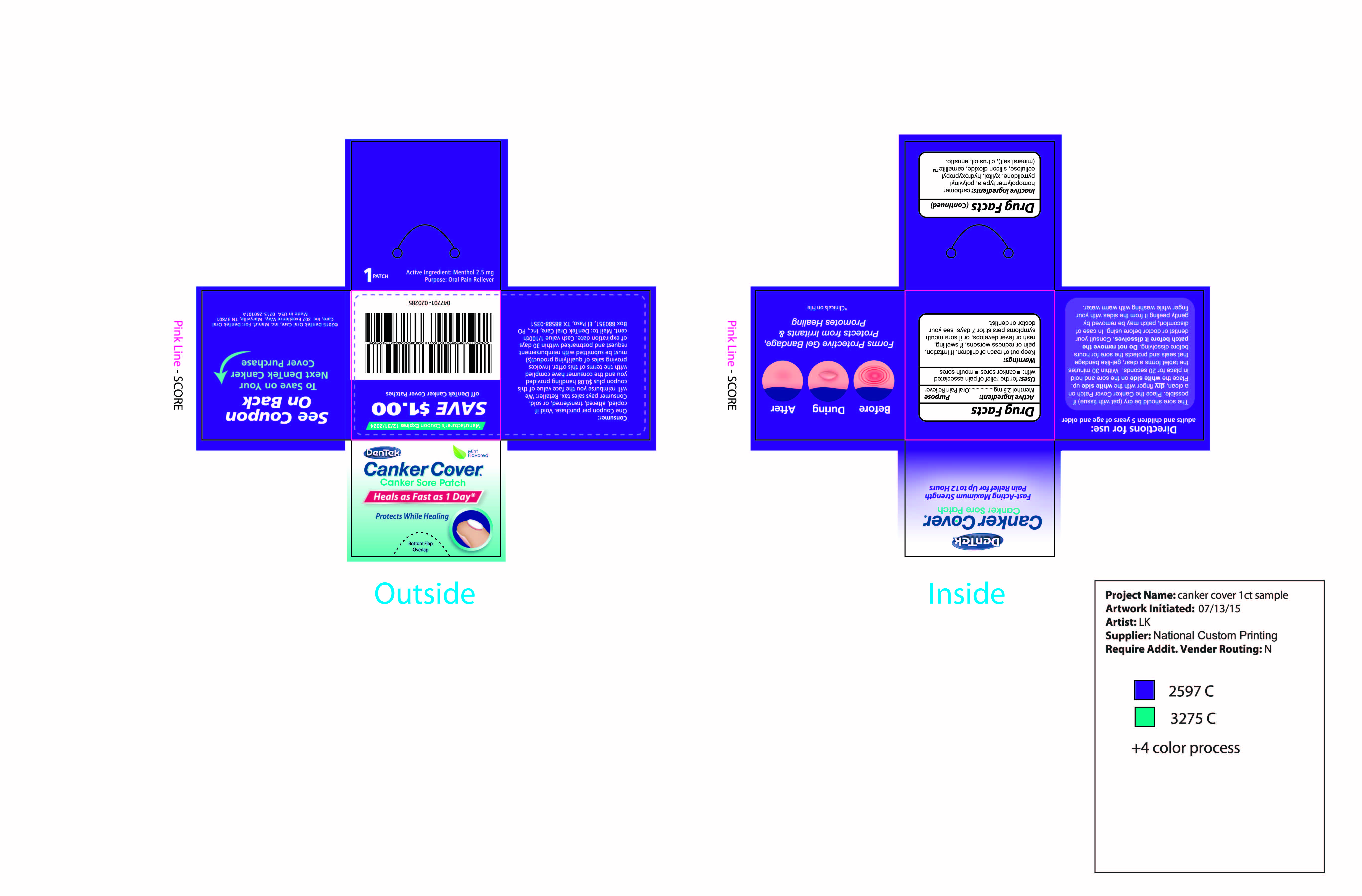 DRUG LABEL: DenTek Canker Cover
NDC: 60630-091 | Form: PATCH, EXTENDED RELEASE
Manufacturer: DenTek Oral Care, Inc.
Category: otc | Type: HUMAN OTC DRUG LABEL
Date: 20151210

ACTIVE INGREDIENTS: MENTHOL 2.5 mg/194.85 mg
INACTIVE INGREDIENTS: SEA SALT 10 mg/194.85 mg; CARBOMER 934 56 mg/194.85 mg; POVIDONE 44 mg/194.85 mg; XYLITOL 65 mg/194.85 mg; HYDROXYPROPYL CELLULOSE (TYPE E) 14 mg/194.85 mg; CITRUS MEDICA FRUIT 2 mg/194.85 mg; COLLOIDAL SILICON DIOXIDE 1.45 mg/194.85 mg; MAGNESIUM STEARATE 0.4 mg/194.85 mg

Canker Cover 1 Count

Active ingredient: (per each patch)

Menthol 2.5 mg

Purpose

Oral Pain Reliever

INDICATIONS AND USAGE

Uses: for the relief of pain associated with: . canker sores . mouth sores

Warnings:

Keep out of reach of children.

Warnings:

If irritation, pain or redness worsens, if swelling, rash or fever develops, or if sore mouth symptoms persist

for 7 days, see your doctor or dentist.

DOSAGE AND ADMINISTRATION

Directions for use: adults and children 5 years of age and older

The sore should be dry (pat with tissue) if possible. Place the Canker Cover Patch on a

clean, dry finger with the white side up. Place the white side on the sore and hold in place

for 20 seconds. Within 30 minutes the tablet forms a clear, gel-like bandage that seals and protects the sore

for hours before dissolving. Do not remove the patch before it dissolves. Consult your dentist or doctor before using.

In case of discomfort, the patch may be removed by gently peeling it from the sides with your finger while

washing with warm water.

INACTIVE INGREDIENT

Inactive ingredients: carbomer homopolymer type a, polyvinyl pyrrolidone, xylitol, hydroxypropyl cellulose, silicon dioxide, carmalliteTM(mineral salt), citrus oil, annatto.